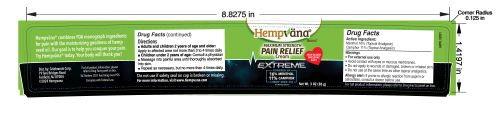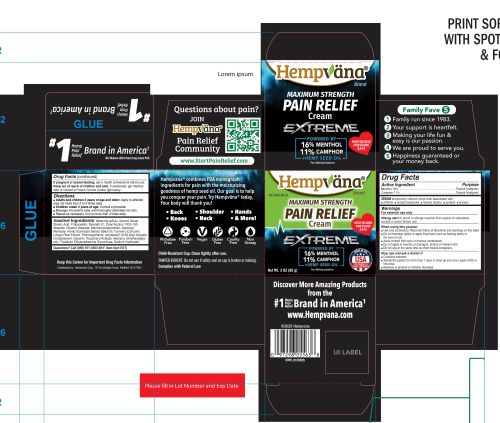 DRUG LABEL: Hempvana Maximum Strength Pain Relief Cream Extreme
NDC: 73287-031 | Form: CREAM
Manufacturer: Telebrands Corp
Category: otc | Type: HUMAN OTC DRUG LABEL
Date: 20250204

ACTIVE INGREDIENTS: MENTHOL 16 g/100 g; CAMPHOR (SYNTHETIC) 11 g/100 g
INACTIVE INGREDIENTS: PEG-100 STEARATE; GLYCERYL MONOSTEARATE; ALLANTOIN; ETHYLHEXYLGLYCERIN; WATER; STEARIC ACID; CANNABIS SATIVA SEED OIL; CURCUMA LONGA (TURMERIC) ROOT; GLYCERIN; SODIUM HYDROXIDE; CETYL ALCOHOL; MENTHOXYPROPANEDIOL; PHENOXYETHANOL; STEARETH-21; ALCOHOL; ISOPROPYL MYRISTATE; ACRYLATES/C10-30 ALKYL ACRYLATE CROSSPOLYMER (60000 MPA.S); .ALPHA.-TOCOPHEROL ACETATE; TRISODIUM ETHYLENEDIAMINE DISUCCINATE; PROPANEDIOL

Hempvana Maximum Strength Pain Relief Cream Extreme

Active Ingredient

Menthol 16%

Camphor 11%

Purpose

Menthol 16%..................Topical Analgesic

Camphor 11%..................Topical Analgesic

Uses

temporarily relieves minor pain associated with:■ arthritis ■ simple backache ■ muscle strains ■ sprains ■ bruises

Warnings

For external use only

Allergy alert:If prone to allergic reaction from aspirin or salicylates, consult a doctor before use.

When using this product

■ Use only as directed. Read and follow all directions and warnings on this label.

■ Do not bandage tightly or apply local heat (such as heating pads) tothe area of use.

■ Avoid contact with eyes or mucous membranes.

■ Do not apply to wounds or damaged, broken or irritated skin.

■ Do not use at the same time as other topical analgesics

Stop use and ask a doctor if

- Condition worsens
- Symptoms persist for more than 7 days or clear up and occur again within a few days
- Redness is present or irritation develops

PREGNANCY OR BREAST FEEDING

If pregnant or breast-feeding, ask a health professional before use.

Keep out of reach of children and pets. If swallowed, get medical help or contact a Poison Control Center right away.

Directions

- Adults and children 2 years of age and older:Apply to affected area not more than 3 to 4 times daily.
- Children under 2 years of age:consult a physician
- Apply generously to affected area.
- Massage into painful area until thoroughly absorbed into skin.
- Repeat as necessary, but no more than 4 times daily.

Inactive Ingredients

Water/Aqua/Eau, Alcohol Denat.,Stearic Acid, Propanediol, Steareth-21, Cetyl Alcohol, PEG-100Stearate, Glyceryl Stearate, Menthoxypropanediol, IsopropylMyristate, Hemp (Cannabis Sativa) Seed Oil, Turmeric (Curcuma
Longa) Root Extract, Phenoxyethanol, Acrylates/C10-30 Alkyl AcrylateCrosspolymer, Glycerin, Tocopheryl Acetate, Allantoin, Ethylhexylglycerin, Trisodium Ethylenediamine Disuccinate, Sodium Hydroxide

Questions?

Questions? Call (855) 877-4503 (M-F, 9am-5pm EST)

PACKAGE LABEL

Hempvana

Maximum Strength

Pain Relief

Cream Extreme

16% Menthol

11% Camphor

+ Hemp Seed Oil for moisturization

Net Wt. 3 OZ (85 g)